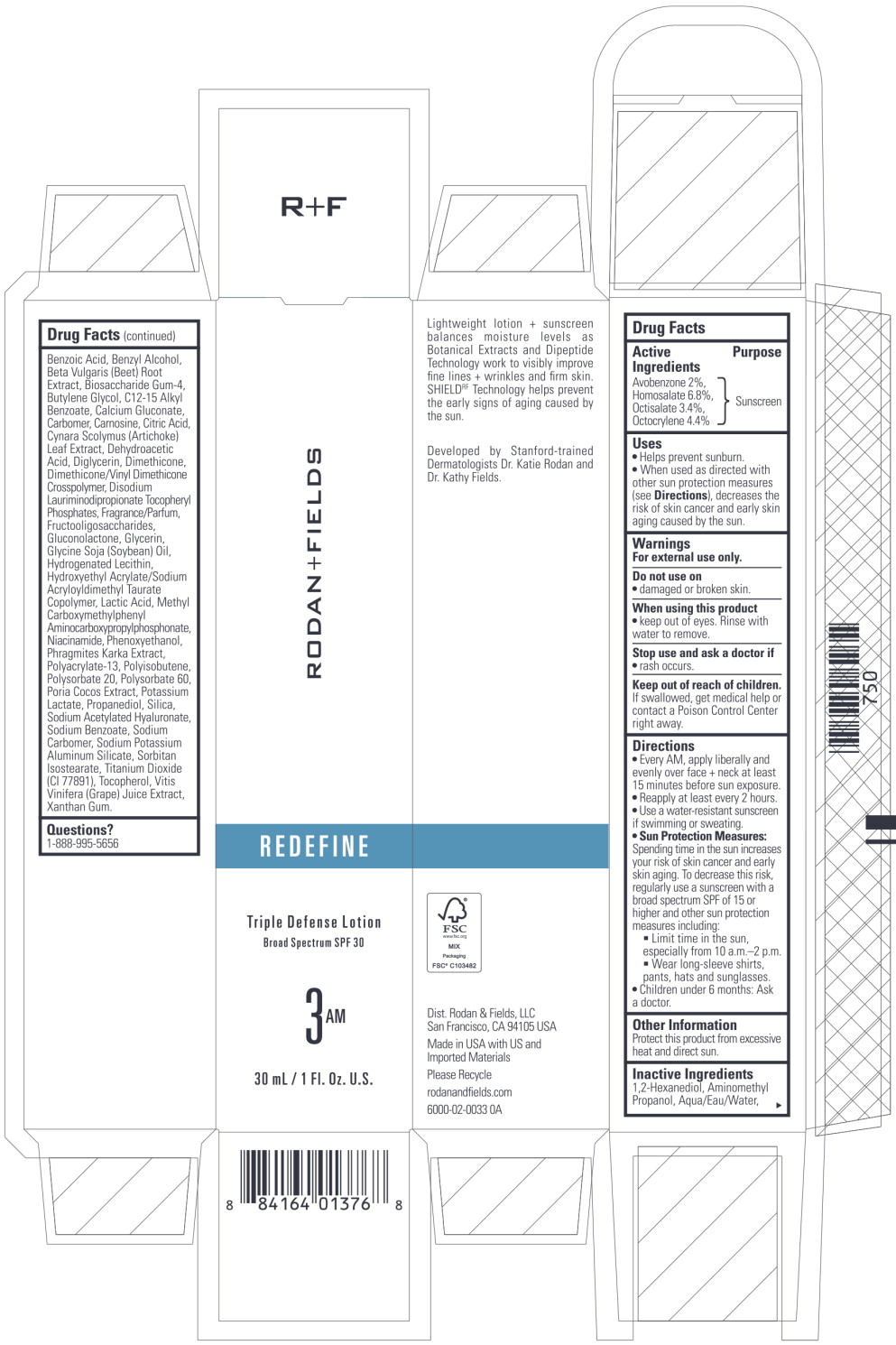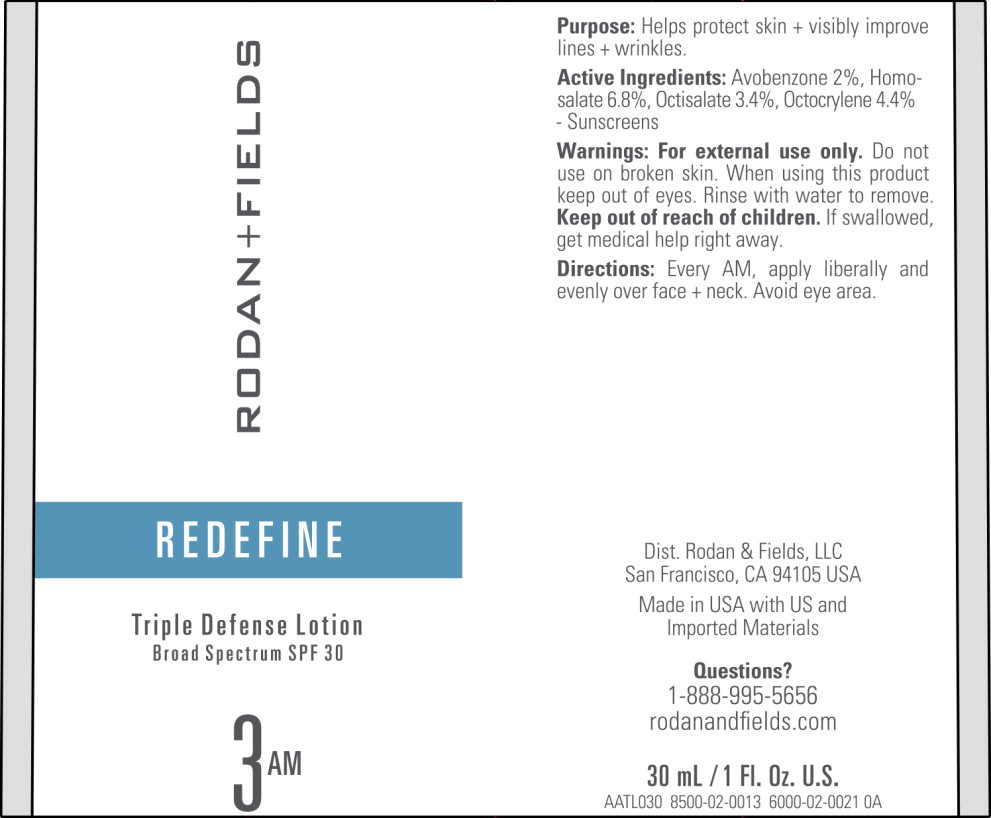 DRUG LABEL: REDEFINE Triple Defense
NDC: 14222-2252 | Form: LOTION
Manufacturer: Rodan & Fields
Category: otc | Type: HUMAN OTC DRUG LABEL
Date: 20231213

ACTIVE INGREDIENTS: AVOBENZONE 0.02 g/1 mL; HOMOSALATE 0.068 g/1 mL; OCTOCRYLENE 0.044 g/1 mL; OCTISALATE 0.034 g/1 mL
INACTIVE INGREDIENTS: WATER; GLYCERIN; ALKYL (C12-15) BENZOATE; SILICON DIOXIDE; NIACINAMIDE; DIMETHICONE; HYDROGENATED SOYBEAN LECITHIN; DIGLYCERIN; BENZYL ALCOHOL; TITANIUM DIOXIDE; PHENOXYETHANOL; BUTYLENE GLYCOL; AMINOMETHYLPROPANOL; TOCOPHEROL; SOYBEAN OIL; SODIUM BENZOATE; XANTHAN GUM; PROPANEDIOL; CARBOXYPOLYMETHYLENE; CARNOSINE; SODIUM ACETYLATED HYALURONATE; POLYISOBUTYLENE (2300 MW); CITRIC ACID MONOHYDRATE; POTASSIUM LACTATE; DISODIUM LAURIMINODIPROPIONATE TOCOPHERYL PHOSPHATES; CYNARA SCOLYMUS LEAF; LACTIC ACID, UNSPECIFIED FORM; SORBITAN ISOSTEARATE; 1,2-HEXANEDIOL; POLYSORBATE 20; BIOSACCHARIDE GUM-4; GLUCONOLACTONE; POLYSORBATE 60; BENZOIC ACID; CALCIUM GLUCONATE; DEHYDROACETIC ACID

Drug Facts

Active Ingredients

Avobenzone 2%,

Homosalate 6.8%,

Octisalate 3.4%,

Octocrylene 4.4%

Purpose

Sunscreen

Uses

- Helps prevent sunburn.
- When used as directed with other sun protection measures (see Directions), decreases the risk of skin cancer and early skin aging caused by the sun.

Warnings

For external use only.

Do not use on

- damaged or broken skin.

When using this product

- keep out of eyes. Rinse with water to remove.

Stop use and ask a doctor if

- rash occurs.

Keep out of reach of children.

If swallowed, get medical help or contact a Poison Control Center right away.

Directions

- Every AM, apply liberally and evenly over face + neck at least 15 minutes before sun exposure.
- Reapply at least every 2 hours.
- Use a water-resistant sunscreen if swimming or sweating.
- Sun Protection Measures:
  Spending time in the sun increases your risk of skin cancer and early skin aging. To decrease this risk, regularly use a sunscreen with a broad spectrum SPF of 15 or higher and other sun protection measures including:

- Limit time in the sun, especially from 10 a.m.-2 p.m.
- Wear long-sleeve shirts, pants, hats and sunglasses.

- Children under 6 months: Ask a doctor.

Other Information

Protect this product from excessive heat and direct sun.

Inactive Ingredients

1,2-Hexanediol, Aminomethyl Propanol, Aqua/Eau/Water, Benzoic Acid, Benzyl Alcohol, Beta Vulgaris (Beet) Root Extract, Biosaccharide Gum-4, Butylene Glycol, C12-15 Alkyl Benzoate, Calcium Gluconate, Carbomer, Carnosine, Citric Acid, Cynara Scolymus (Artichoke) Leaf Extract, Dehydroacetic Acid, Diglycerin, Dimethicone, Dimethicone/Vinyl Dimethicone Crosspolymer, Disodium Lauriminodipropionate Tocopheryl Phosphates, Fragrance/Parfum, Fructooligosaccharides, Gluconolactone, Glycerin, Glycine Soja (Soybean) Oil, Hydrogenated Lecithin, Hydroxyethyl Acrylate/Sodium Acryloyldimethyl Taurate Copolymer, Lactic Acid, Methyl Carboxymethylphenyl Aminocarboxypropylphosphonate, Niacinamide, Phenoxyethanol, Phragmites Karka Extract, Po yacrylate-13, Polyisobutene, Po ysorbate 20, Polysorbate 60, Poria Cocos Extract, Potassium Lactate, Propanediol, Silica, Sodium Acetylated Hyaluronate, Sodium Benzoate, Sodium Carbomer, Sodium Potassium Aluminum Silicate, Sorbitan Isostearate, Titanium Dioxide (Cl 77891), Tocopherol, Vitis Vinifera (Grape) Juice Extract, Xanthan Gum.

Questions?

1-888-995-5656

Principal Display Panel – 30 mL Carton Label

RODAN + FIELDS

REDEFINE

Triple Defense Lotion
Broad Spectrum SPF 30

3 AM

30 mL/1 Fl. Oz. U.S.

Principal Display Panel – 30 mL Bottle Pump Label

RODAN + FIELDS

REDEFINE

Triple Defense Lotion Broad Spectrum SPF 30

3 AM